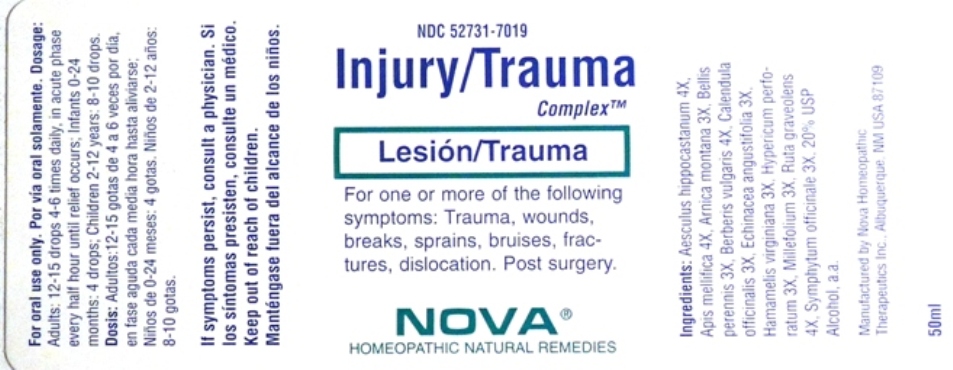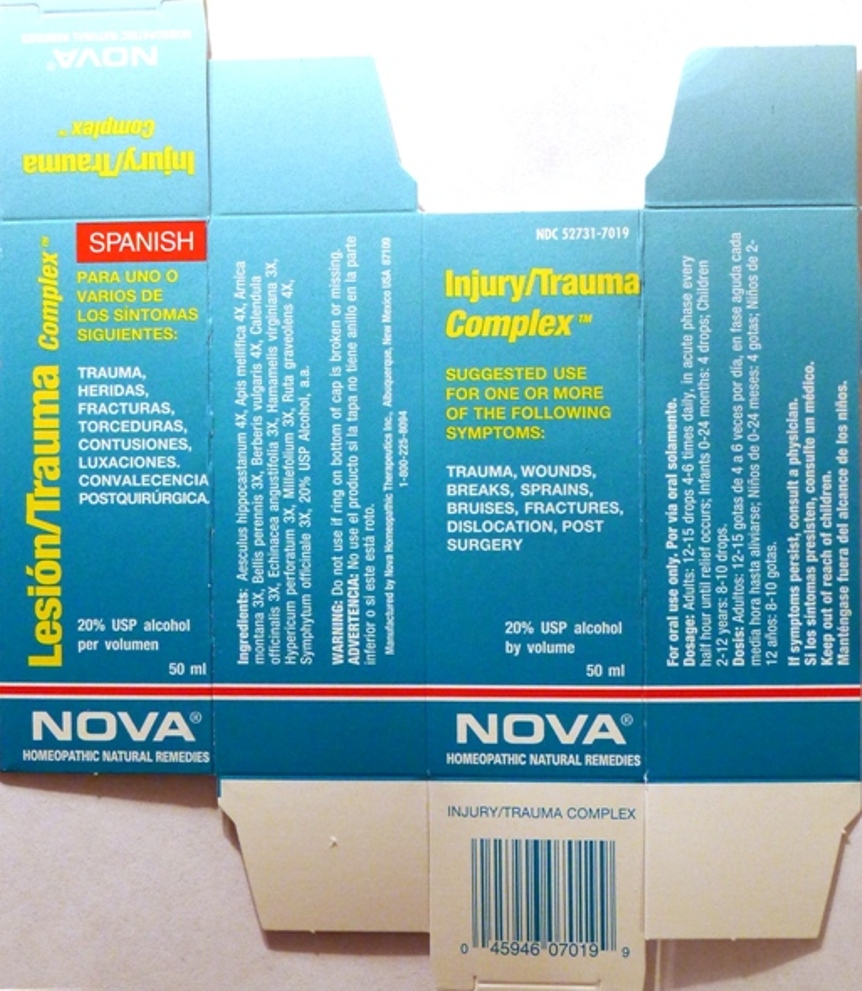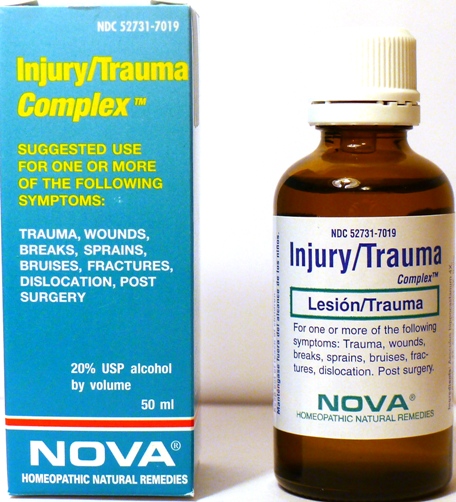 DRUG LABEL: Injury/Trauma Complex
NDC: 52731-7019 | Form: LIQUID
Manufacturer: Nova Homeopathic Therapeutics, Inc.
Category: homeopathic | Type: HUMAN OTC DRUG LABEL
Date: 20110601

ACTIVE INGREDIENTS: HORSE CHESTNUT 4 [hp_X]/1 mL; APIS MELLIFERA 4 [hp_X]/1 mL; ARNICA MONTANA 3 [hp_X]/1 mL; BELLIS PERENNIS 3 [hp_X]/1 mL; BERBERIS VULGARIS ROOT BARK 4 [hp_X]/1 mL; CALENDULA OFFICINALIS FLOWERING TOP 3 [hp_X]/1 mL; ECHINACEA ANGUSTIFOLIA 3 [hp_X]/1 mL; HAMAMELIS VIRGINIANA ROOT BARK/STEM BARK 3 [hp_X]/1 mL; HYPERICUM PERFORATUM 3 [hp_X]/1 mL; ACHILLEA MILLEFOLIUM 3 [hp_X]/1 mL; RUTA GRAVEOLENS FLOWERING TOP 4 [hp_X]/1 mL; COMFREY LEAF 3 [hp_X]/1 mL
INACTIVE INGREDIENTS: ALCOHOL

Injury/Trauma Complex

Purpose:

Suggested use for one or more of the following symptoms:

Trauma, wounds, breaks, sprains, bruises, fractures, dislocation, post surgery.

Usage and Dosage:

For oral use only.

DOSAGE AND ADMINISTRATION

Adults:
In Acute Phase:
12-15 drops, every half hour until relief occurs
When Relief Occurs:
12-15 drops, 4-6 times per day
Children 2-12 years:
8-10 drops, 4-6 times per day

Infants 0 - 24 months:

4 drops, 4-6 times per day

Warnings:

Keep out of reach of children.

WARNINGS

If symptoms persist, consult a physician.
Do not use if ring on bottom of cap is broken or missing.

Active Ingredients:

Aesculus hippocastanum 4X, Apis mellifica 4X, Arnica montana 3X, Bellis perennis 3X, Berberis vulgaris 4X, Calendula officinalis 3X, Echinacea angustifolia 3X, Hamamelis virginiana 3X, Hypericum perforatum 3X, Millefolium 3X, Ruta graveolens 4X, Symphytum officinale 3X

Inactive Ingredients:

Alcohol, 20% USP

QUESTIONS

Manufactured by Nova Homeopathic Therapeutics Inc., Albuquerque, New Mexico USA 87109
1-800-225-8094

PACKAGE LABEL

Injury/Trauma Complex Product

Injury/Trauma Complex Bottle Label

Injury/Trauma Complex Box